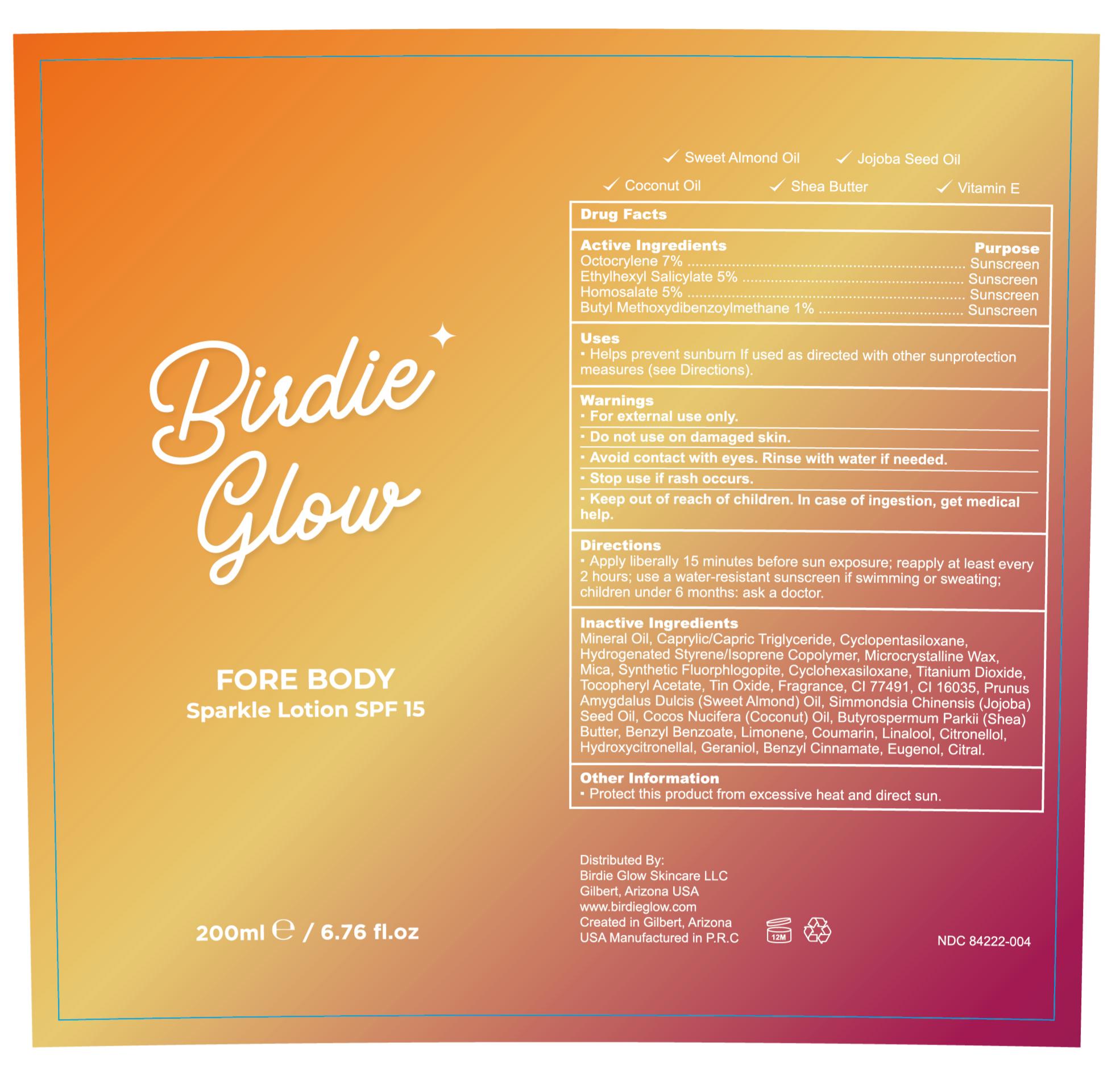 DRUG LABEL: Birdie Glow SparkleLotion SPF 15
NDC: 84222-004 | Form: OIL
Manufacturer: Foshan Miwei Cosmetics Co., Ltd.
Category: otc | Type: HUMAN OTC DRUG LABEL
Date: 20250928

ACTIVE INGREDIENTS: ETHYLHEXYL SALICYLATE 5 g/100 mL; OCTOCRYLENE 7 g/100 mL; HOMOSALATE 5 g/100 mL; BUTYL METHOXYDIBENZOYLMETHANE 1 g/100 mL
INACTIVE INGREDIENTS: JOJOBA OIL 0.5 mL/100 mL; FRAGRANCE 13576 0.72446 mL/100 mL; TITANIUM DIOXIDE 1.0904 mL/100 mL; CAPRYLIC/CAPRIC TRIGLYCERIDE 10 mL/100 mL; MICA 2.8913 mL/100 mL; CYCLOHEXASILOXANE 2 mL/100 mL; SHEA BUTTER 0.5 mL/100 mL; CI 16035 0.5742 mL/100 mL; BENZYL BENZOATE 0.14156 mL/100 mL; LIMONENE, (+)- 0.04386 mL/100 mL; LINALOOL, (+/-)- 0.02287 mL/100 mL; EUGENOL 0.00214 mL/100 mL; COUMARIN 0.028 mL/100 mL; CITRAL 0.00183 mL/100 mL; MICROCRYSTALLINE WAX 3 mL/100 mL; GERANIOL 0.00518 mL/100 mL; STYRENE/ISOPRENE COPOLYMER (28:72; 210000 MW) 4.688 mL/100 mL; .BETA.-CITRONELLOL, (R)- 0.0201 mL/100 mL; BENZYL CINNAMATE 0.004 mL/100 mL; MINERAL OIL 42.192 mL/100 mL; CYCLOPENTASILOXANE 8 mL/100 mL; MAGNESIUM POTASSIUM ALUMINOSILICATE FLUORIDE 2.0097 mL/100 mL; ALMOND OIL 0.5 mL/100 mL; COCONUT OIL 0.5 mL/100 mL; .ALPHA.-TOCOPHEROL ACETATE 1 mL/100 mL; TIN OXIDE 0.8468 mL/100 mL; CI 77491 0.7076 mL/100 mL; HYDROXYCITRONELLAL 0.006 mL/100 mL

Birdie Glow Sparkle Lotion SPF 15

Drug Facts

Active Ingredients Purpose

Octocrylene 7% ................................................... Sunscreen

Ethylhexyl Salicylate 5% ..................................... Sunscreen

Homosalate 5% ................................................... Sunscreen

Butyl Methoxydibenzoylmethane 1% .................. Sunscreen

Uses

· Helps prevent sunburn, decreases the risk of skin cancer and early skin aging if used as directed.

· Adds a shimmery glow for on and off the golf course.

Warnings

· For external use only.

· Do not use on damaged skin.

· Avoid contact with eyes. Rinse with water if needed.

· Stop use if rash occurs.

· Keep out of reach of children. In case of ingestion, get medical help.

Keep out of reach of children. In case of ingestion, get medical help.

DOSAGE AND ADMINISTRATION

How to Apply

Apply generously to the body for a luminous shimmer and protective layer that makes your skin glow. The natural ingredients provide additional sun protection.

This SPF 15 lotion offers sun protection with a natural shimmer and tint.

Embrace the sun safely with our blend of nourishing oils.

INACTIVE INGREDIENT

Mineral Oil, Caprylic/Capric Triglyceride, Cyclopentasiloxane, Hydrogenated Styrene/Isoprene Copolymer, Microcrystalline Wax, Mica, Synthetic Fluorphlogopite, Cyclohexasiloxane, Titanium Dioxide, Tocopheryl Acetate, Tin Oxide, Fragrance, CI 77491, CI 16035, Prunus Amygdalus Dulcis (Sweet Almond) Oil, Simmondsia Chinensis (Jojoba) Seed Oil, Cocos Nucifera (Coconut) Oil, Butyrospermum Parkii (Shea) Butter, Benzyl Benzoate, Limonene, Coumarin, Linalool, Citronellol, Hydroxycitronellal, Geraniol, Benzyl Cinnamate, Eugenol, Citral

Other information

· Protect this product from excessive heat and direct sun.